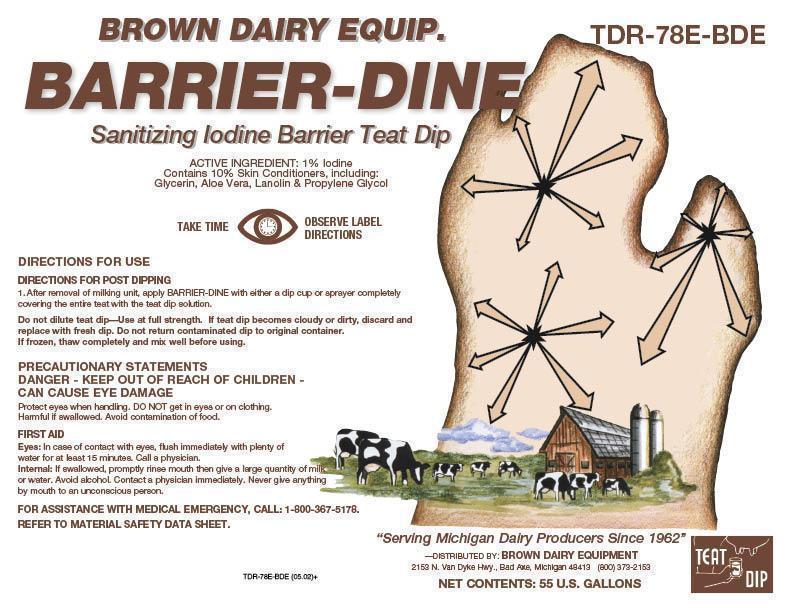 DRUG LABEL: BARRIER-DINE
NDC: 62897-780 | Form: SOLUTION
Manufacturer: Brown Dairy Equipment
Category: animal | Type: OTC ANIMAL DRUG LABEL
Date: 20130108

ACTIVE INGREDIENTS: IODINE 10 g/1 L

BARRIER-DINE

Brown Dairy Equip.

BARRIER-DINE

Sanitizing Iodine Barrier Teat Dip

ACTIVE INGREDIENT: 1% Iodine

Contains 10% Skin Conditioners. including:

Glycerin, Aloe Vera, Lanolin & Propylene Glycol

DIRECTIONS FOR USE

DIRECTIONS FOR POST DPPING

1. After removal of milking unit, apply BARRIER-DINE with either a dip cup or sprayer completely covering the entire teat with the teat dip solution.

Do not dilute teat dip—Use at full strength. If teat dip becomes cloudy or dirty, discard and replace with fresh dip. Do not return contaminated dip to original container.

If frozen, thaw completely and mix well before using.

PRECAUTIONARY STATEMENTS

DANGER - KEEP OUT OF REACH OF CHILDREN

CAN CAUSE EYE DAMAGE.

Protect eyes when handling. DO NOT get in eyes or on clothing.

Harmful is swallowed. Avoid contamination of food.

FIRST AID

Eyes: In case of contact with eyes, flush immediately with plenty of water for at least 15 minutes. Call a physician.

Internal: If swallowed, promptly rinse mouth with water then give a large quantity of milk or water. Avoid alcohol. Contact a physician immediately. Never give anything by mouth to an unconscious person.

FOR ASSISTANCE WITH MEDICAL EMERGENCY, CALL 1-800-367-5178.

REFER TO MATERIAL DATA SAFETY SHEET.

PRINCIPAL DISPLAY PANEL/REPRESENTATIVE LABEL

Brown Dairy Equip.

BARRIER-DINE

Sanitizing Iodine Barrier Teat Dip

ACTIVE INGREDIENT: 1% Iodine

Contains 10% Skin Conditioners. including:

Glycerin, Aloe Vera, Lanolin & Propylene Glycol

TAKE TIME OBSERVE LABEL DIRECTIONS

“Serving Michigan Dairy Producers Since 1962”

Distributed by: Brown Dairy Equipment

2152 N. Van Dyke Hwy., Bad Axe, Michigan 48413 (800) 373-2153

NET CONTENTS: 55 U.S. GALLONS